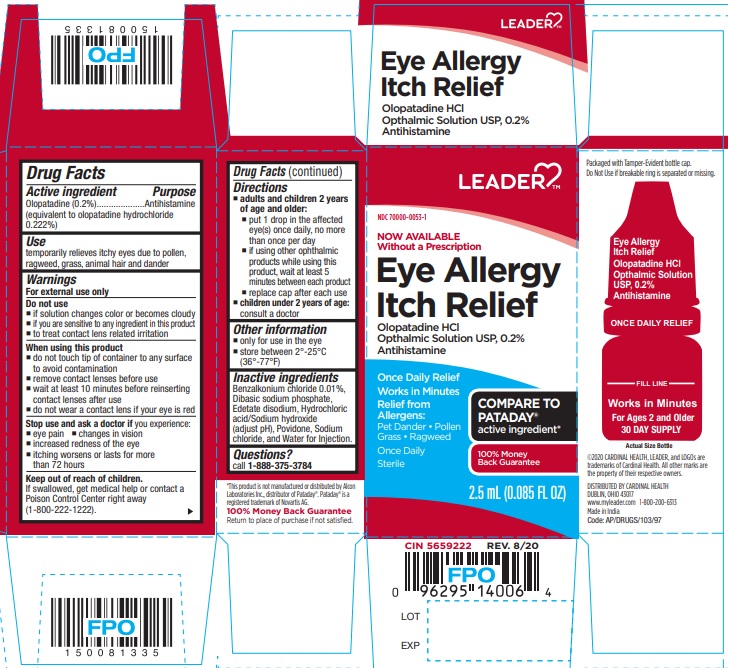 DRUG LABEL: Eye Allergy Itch Relief
NDC: 70000-0053 | Form: SOLUTION
Manufacturer: CARDINAL HEALTH 110, LLC. DBA LEADER
Category: otc | Type: Human OTC Drug Label
Date: 20251212

ACTIVE INGREDIENTS: OLOPATADINE HYDROCHLORIDE 2 mg/1 mL
INACTIVE INGREDIENTS: BENZALKONIUM CHLORIDE; SODIUM PHOSPHATE, DIBASIC, ANHYDROUS; EDETATE DISODIUM; HYDROCHLORIC ACID; POVIDONE K30; SODIUM CHLORIDE; SODIUM HYDROXIDE; WATER

ACTIVE INGREDIENT

Olopatadine (0.2%) (equivalent to olopatadine hydrochloride 0.222%)

PURPOSE

Antihistamine

USE

temporarily relieves itchy eyes due to pollen, ragweed, grass, animal hair and dander

WARNINGS

For external use only

DO NOT USE

- if solution changes color or becomes cloudy
- if you are sensitive to any ingredient in this product
- to treat contact lens related irritation

WHEN USING THIS PRODUCT

- do not touch tip of container to any surface to avoid contamination
- remove contact lenses before use
- wait at least 10 minutes before reinserting contact lenses after use
- do not wear a contact lens if your eye is red

STOP USE AND ASK DOCTOR IF

you experience:

- eye pain
- changes in vision
- increased redness of the eye
- itching worsens or lasts for more than 72 hours

KEEP OUT OF REACH OF CHILDREN

If swallowed, get medical help or contact a Poison Control Center right away.

DIRECTIONS

- adults and children 2 years of age and older:
- put 1 drop in the affected eye(s) once daily, no more than once per day
- if using other ophthalmic products while using this product, wait at least 5 minutes between each product
- replace cap after each use
- children under 2 years of age: consult a doctor

OTHER INFORMATION

• only for use in the eye
• store between 2° to 25°C (36° to 77°F)

INACTIVE INGREDIENTS

Benzalkonium chloride 0.01%, Dibasic sodium phosphate, Edetate disodium, Hydrochloric acid/Sodium hydroxide (adjust pH), Povidone, Sodium chloride, and Water for Injection.

QUESTIONS?

Call 1-888-375-3784

PRINCIPAL DISPLAY PANEL

NOW AVAILABLE Without a Prescription

Eye Allergy Itch Relief

Olopatadine HCl Opthalmic Solution USP, 0.2%

Antihistamine

Once Daily Relief

Works in Minutes

Relief from Allergens:

Pet Dander • Pollen • Grass • Ragweed

Once Daily

Sterile

2.5 mL (0.085 FL OZ)

For Ages 2 and Older

30 DAY SUPPLY

Packaged with Tamper-Evident bottle cap. Do Not Use if breakable ring is separated or missing.

COMPARE TO PATADAY® active ingredient*

©2020 CARDINAL HEALTH, LEADER, and LOGOs are trademarks of Cardinal Health. All other marks are the property of their respective owners.

DISTRIBUTED BY

CARDINAL HEALTH

DUBLIN, OHIO 43017

www.myleader.com 1-800-200-6313

Made in India

Code: AP/DRUGS/103/97

*This product is not manufactured or distributed by Alcon Laboratories Inc., distributor of Pataday®. Pataday® is a registered trademark of Novartis AG.